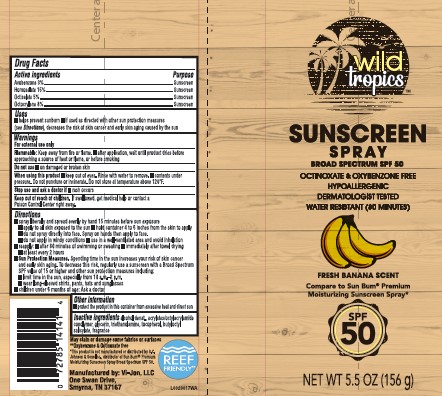 DRUG LABEL: Sunscreen SPF50
NDC: 11344-055 | Form: SPRAY
Manufacturer: Consumer Product Partners, LLC
Category: otc | Type: HUMAN OTC DRUG LABEL
Date: 20250701

ACTIVE INGREDIENTS: AVOBENZONE 30 mg/1 g; HOMOSALATE 150 mg/1 g; OCTISALATE 50 mg/1 g; OCTOCRYLENE 80 mg/1 g
INACTIVE INGREDIENTS: ALCOHOL; ACRYLATE/ISOBUTYL METHACRYLATE/N-TERT-OCTYLACRYLAMIDE COPOLYMER (40000 MW); GLYCERIN; TROLAMINE; TOCOPHEROL; BUTYLOCTYL SALICYLATE

Wild Tropics 055.000/055AA
SPF 50 Sunscreen Spray

Active ingredients

Avobenzone 3%

Homosalate 15%

Octisalate 5%

Octocrylene 8%

Purpose

Sunscreen

Uses

- helps prevent sunburn
- if used as directed with other sun protection measures (see Directions), decreases the risk of skin cancer and early skin aging caused by the sun

Warnings

For external use only

Flammable:

Keep away from fire or flame.

- after application, wait until product dries before approacing a souce of heat or flame, or before smoking

Do not use

- on damaged or broken skin

When using this product

- keep out of eyes. Rinse with water to remove.
- contents under pressure. Do not puncture or incinerate. Do not store at temperature above 120ºF.

Stop use and ask a doctor if

- rash occurs

Keep out of reach of children.

If swallowed, get medical help or contact a Poison Conrol Center right away.

Direction

■ spray liberally and spread evenly by hand 15 minutes before sun exposure
■ apply to all skin exposed to the sun
■ hold container 4 to 6 inches from the skin to apply
■ do not spray directly into face. Spray on hands then apply to face.
■ do not apply in windy conditions
■ use in a well-ventilated area and avoid inhalation
■ reapply:
■ after 80 minutes of swimming or sweating
■ immediately after towel drying
■ at least every 2 hours
■ Sun Protection Measures. Spending time in the sun increases your risk of skin cancer and early skin aging. To decrease this risk, regularly use a sunscreen with a Broad Spectrum SPF value of 15 or higher and other sun protection measures including:
■ limit time in the sun, especially from 10 a.m.–2 p.m.
■ wear long-sleeved shirts, pants, hats and sunglasses
■ children under 6 months of age: Ask a doctor

Other information

- protect the product in this container from excessive heat and direct sun

Inactive ingredients

alcohol denat., acrylates/octylacrylamide copolymer, glycerin, triethanolamine, tocopherol, butyloctyl salicylate, fragrance

Claims and Disclaimer

May stain or damage some fabrics of surfaces

**Oxybenzone & Octinoxate free

*This product is not manufactured or distributed by S.C. Johnson & Sons, Inc., distributor of Sun Bum® Premium Moisturizing Sunscreen Spray Broad Spectrum SPF 50.

REEF FRIENDLY**

Adverse reaction

Manufactured by: Vi-Jon, LLC

One Swan Drive,

Smynra, 37167

Principal display panel

Wild Tropics™

SUNSCREEN SPRAY

BROAD SPECTRUM SPF 50

OCTINOXATE & OXYBENZONE FREE

HYPOALLERGENIC

DERMATOLOGIST TESTED

WATER RESISTANT (80 MINUTES)

FRESH BANANA SCENT

Compare to Sun Bum®Premium Moisturizing Sunscreen Spray*

SPF 50

NET WT 5.5 OZ (156 g)